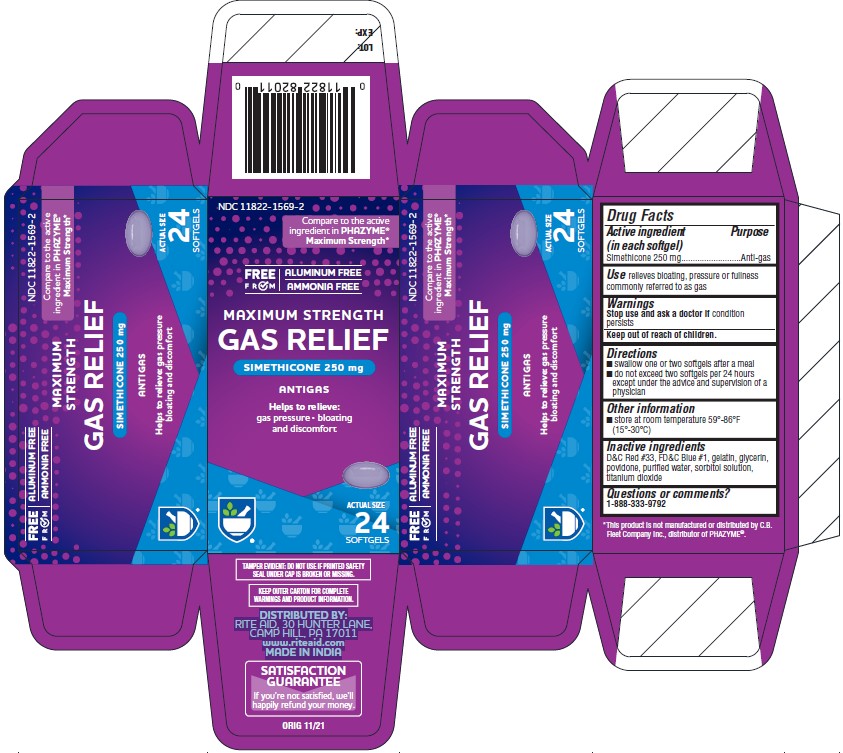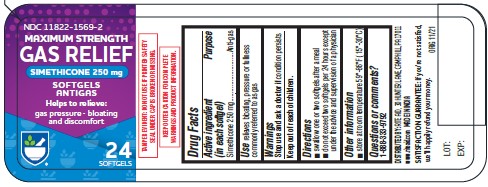 DRUG LABEL: Simethicone
NDC: 11822-1569 | Form: CAPSULE, LIQUID FILLED
Manufacturer: RITE AID CORPORATION
Category: otc | Type: HUMAN OTC DRUG LABEL
Date: 20241230

ACTIVE INGREDIENTS: DIMETHICONE 250 mg/1 1
INACTIVE INGREDIENTS: D&C RED NO. 33; FD&C BLUE NO. 1; GELATIN; GLYCERIN; POVIDONE; WATER; SORBITOL; TITANIUM DIOXIDE

MAXIMUM STRENGTH
GAS RELIEF

Active Ingredient (in each softgel)

Simethicone 250 mg

Purpose

Anti-gas

Uses

relives bloating, pressure or fullness commonly referred to as gas

Warnings

Stop use and ask a doctor if condition persists

Keep out of reach of children

Directions

• Swallow one or two softgels after a mea • do not exceed two softgels in 24 hours except under the advice and supervision of a physician

Other Information

• store at room temperature 59-86°F (15-30°C)

Inactive ingredients

D&C Red #33, FD&C Blue #1, gelatin, glycerin, povidone, purified water, sorbitol solution, titanium dioxide

Questions or comments?

1-888-333-9792

Distributed by:
RITE AID
30 Hunter Lane, Camp Hill, PA 17011
www.riteaid.com
Made in India